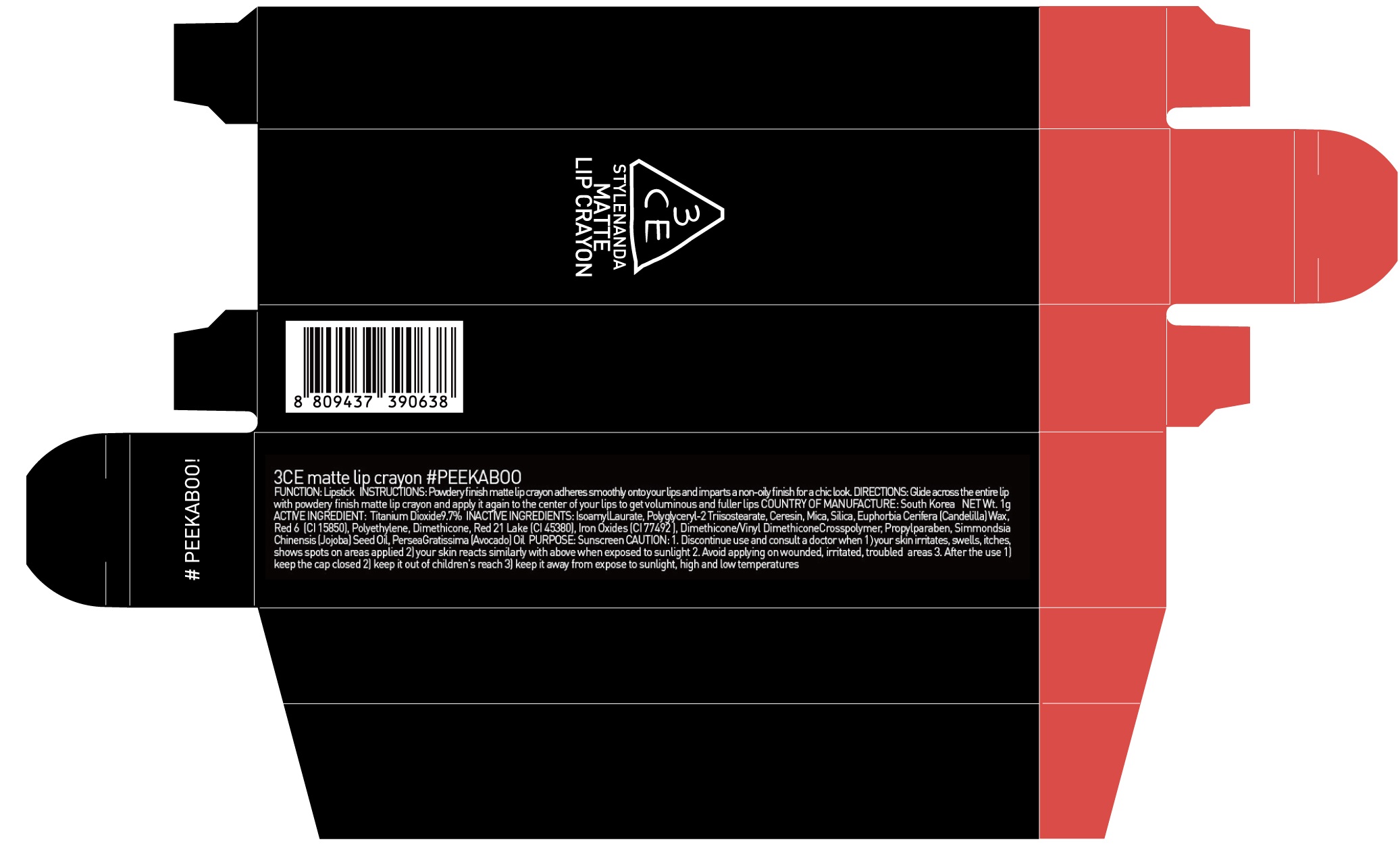 DRUG LABEL: 3CE MATTE LIP CRAYON PEEKABOO
NDC: 60764-090 | Form: LIPSTICK
Manufacturer: Nanda Co., Ltd
Category: otc | Type: HUMAN OTC DRUG LABEL
Date: 20161011

ACTIVE INGREDIENTS: Titanium Dioxide 0.097 g/1 g
INACTIVE INGREDIENTS: Isoamyl Laurate; Ceresin

ACTIVE INGREDIENT

Active Ingredient: Titanium Dioxide 9.7%

INACTIVE INGREDIENT

Inactive Ingredients: Isoamyl Laurate, Polyglyceryl-2 Triisostearate, Ceresin, Mica, Silica, Euphorbia Cerifera (Candelilla) Wax, Red 6 (CI 15850), Polyethylene, Dimethicone, Red 21 Lake (CI 45380), Iron Oxides (CI 77492), Dimethicone/Vinyl DimethiconeCrosspolymer, Propylparaben, SimmondsiaChinensis (Jojoba) Seed Oil, PerseaGratissima (Avocado) Oil

PURPOSE

Purpose: Sunscreen

CAUTION

CAUTION: 1. Discontinue use and consult a doctor when - your skin irritates, swells, itches, shows spots on areas applied - your skin reacts similarly with above when exposed to sunlight 2. Avoid applying on wounded, irritated, troubled areas 3. After the use - keep the cap closed - keep it out of children's reach - keep it away from expose to sunlight, high and low temperatures

DESCRIPTION

INSTRUCTIONS: Powdery finish matte lip crayon adheres smoothly onto your lips and imparts a non-oily finish for a chic look.

Directions: Glide across the entire lip with powdery finish matte lip crayon and apply it again to the center of your lips to get voluminous and fuller lips